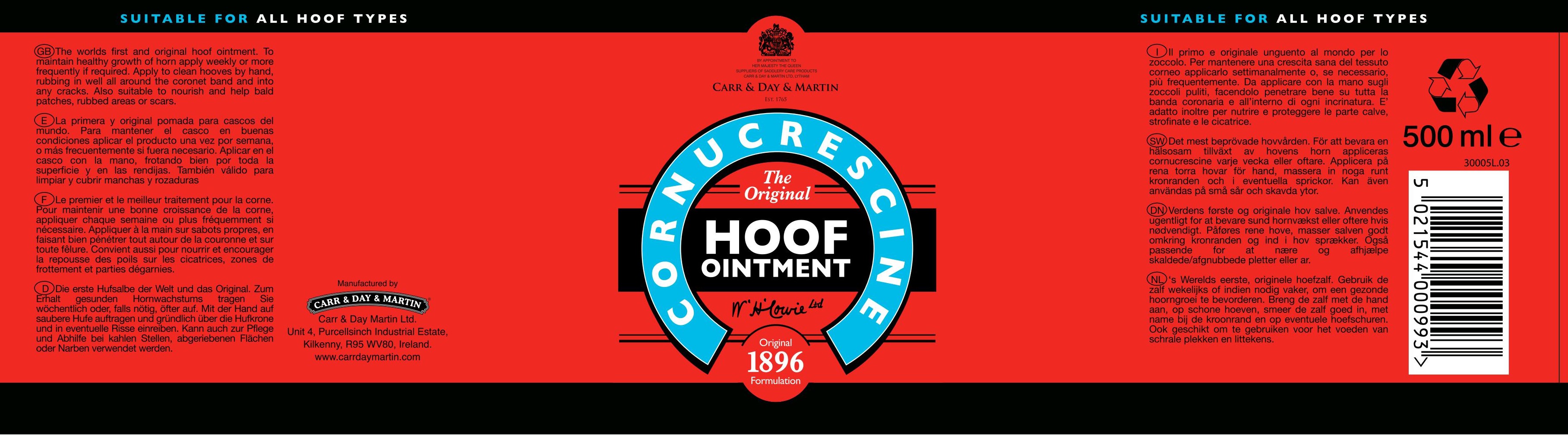 DRUG LABEL: Cornucrescine Original Hoof
NDC: 43258-302 | Form: OINTMENT
Manufacturer: Carr & Day & Martin Unlimited Company
Category: animal | Type: OTC ANIMAL DRUG LABEL
Date: 20241223

ACTIVE INGREDIENTS: PETROLATUM 731 g/1 L; Sassafras Oil 10.1 g/1 L

Cornucrescine The Original Hoof Ointment

INDICATIONS AND USAGE

To maintain healthy growth of horn apply weekly or more frequently if required.

Also suitable to nourish and help bald patches, rubbed areas or scars.

DOSAGE AND ADMINISTRATION

Apply to clean hooves by hand, rubbing in well all around the coronet band and into any cracks.

Manufactured by

Carr & Day & Martin Unlimited Company

Unit 4, Purcellsinch Industrial Estate,

Kilkenny, R95 WV80, Ireland.

www.carrdaymartin.com